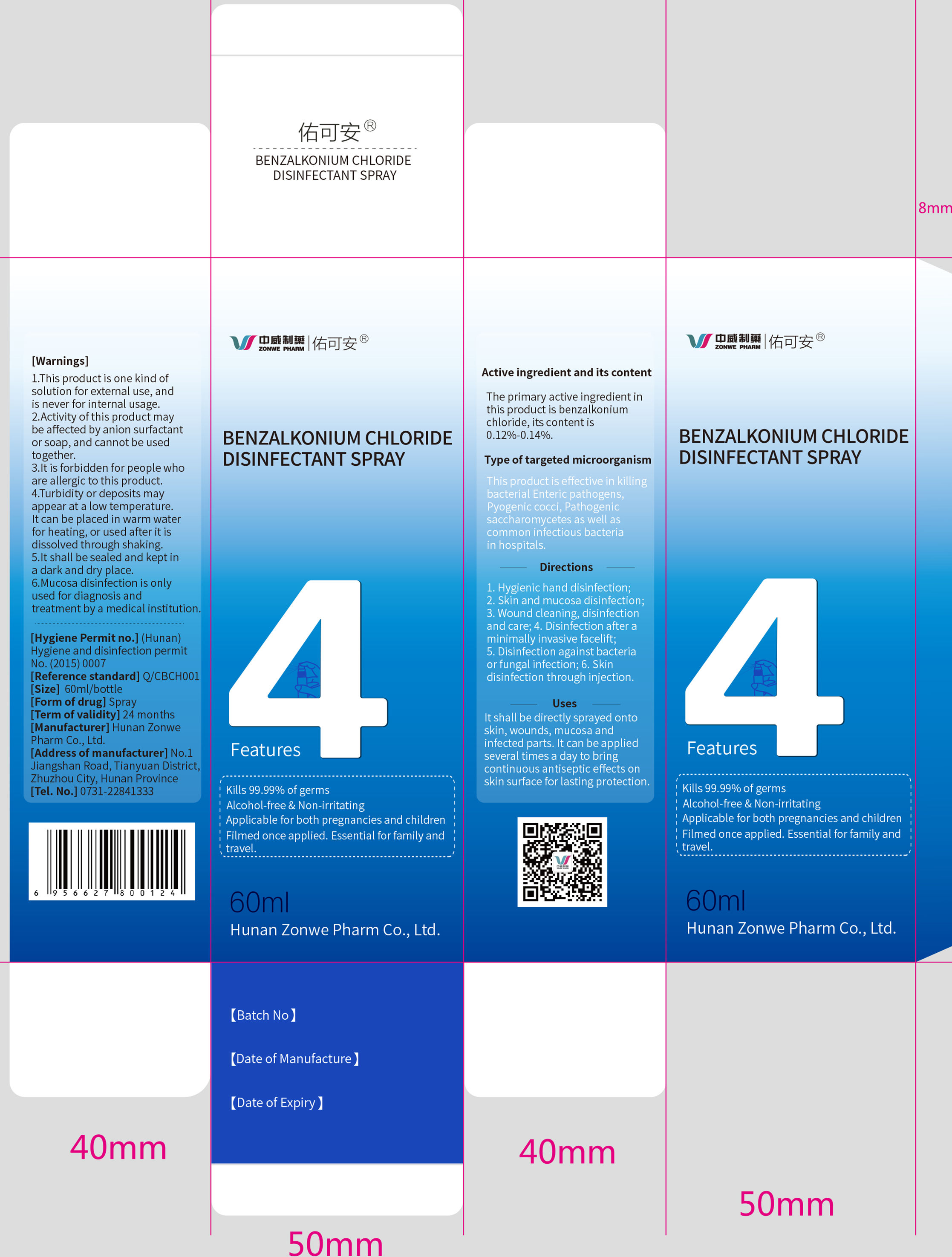 DRUG LABEL: Youke an
NDC: 54749-001 | Form: LIQUID
Manufacturer: HUNAN ZONWE PHARMACEUTICAL CO., LTD.
Category: otc | Type: HUMAN OTC DRUG LABEL
Date: 20201120

ACTIVE INGREDIENTS: BENZALKONIUM 0.072 mg/60 mL
INACTIVE INGREDIENTS: PROPYLENE GLYCOL; SODIUM PHOSPHATE, MONOBASIC, DIHYDRATE; SODIUM PHOSPHATE DIBASIC DIHYDRATE; WATER; EDETATE DISODIUM

ACTIVE INGREDIENT

benzalkonium chloride

keep out of children

PURPOSE

Kills 99.99% of germs

DOSAGE AND ADMINISTRATION

a little

INDICATIONS AND USAGE

It shall be directly sprayed onto skin, wounds, mucosa and infected parts. It can be applied several times a day to bring continuous antiseptic effects on skin surface for lasting protection.

INACTIVE INGREDIENT

Propylene glycol

Sodium dihydrogen phosphate dihydrate

Disodium hydrogen phosphate

Disodium edetate, dihydrate

water

WARNINGS

1.This product is one kind of solution for external use, and is never for internal usage.
2.Activity of this product may be affected by anion surfactant or soap, and cannot be used together.
3.It is forbidden for people who are allergic to this product.
4.Turbidity or deposits may appear at a low temperature. It can be placed in warm waterfor heating, or used after it is dissolved through shaking.
5.It shall be sealed and kept in a dark and dry place.
6.Mucosa disinfection is only used for diagnosis and treatment by a medical institution.